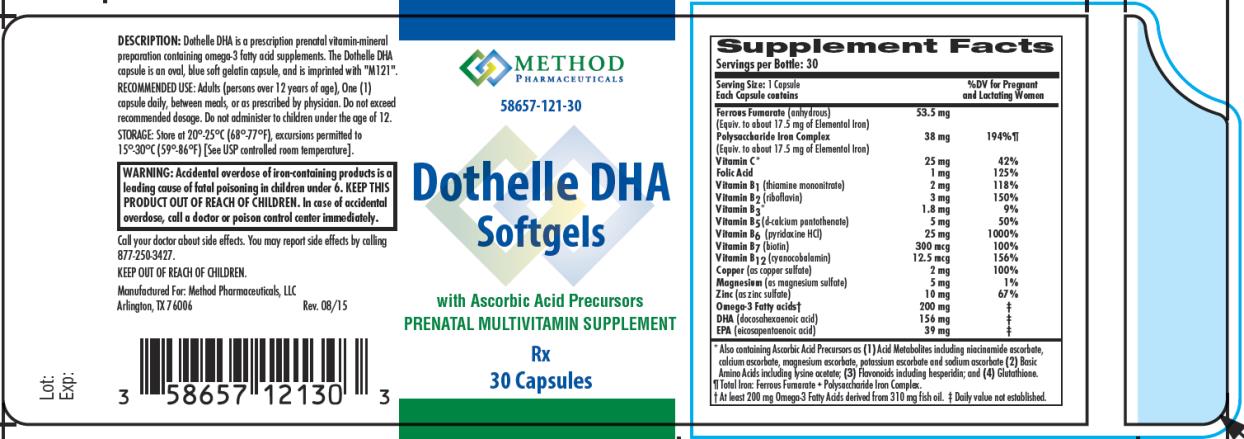 DRUG LABEL: Dothelle DHA
NDC: 58657-121 | Form: CAPSULE, LIQUID FILLED
Manufacturer: Method Pharmaceuticals, LLC
Category: other | Type: DIETARY SUPPLEMENT
Date: 20150820

ACTIVE INGREDIENTS: FERROUS FUMARATE 53.5 mg/1 1; IRON 38 mg/1 1; ASCORBIC ACID 25 mg/1 1; FOLIC ACID 1 mg/1 1; THIAMINE MONONITRATE 2 mg/1 1; RIBOFLAVIN 3 mg/1 1; NIACIN 1.8 mg/1 1; CALCIUM PANTOTHENATE 5 mg/1 1; PYRIDOXINE HYDROCHLORIDE 25 mg/1 1; BIOTIN 300 ug/1 1; CYANOCOBALAMIN 12.5 ug/1 1; CUPRIC SULFATE 2 mg/1 1; MAGNESIUM SULFATE, UNSPECIFIED FORM 5 mg/1 1; ZINC SULFATE, UNSPECIFIED FORM 10 mg/1 1; OMEGA-3 FATTY ACIDS 200 mg/1 1; DOCONEXENT 156 mg/1 1; ICOSAPENT 39 mg/1 1
INACTIVE INGREDIENTS: GELATIN; GLYCERIN; LECITHIN, SOYBEAN; YELLOW WAX; LYSINE ACETATE; CITRUS BIOFLAVONOIDS; FD&C BLUE NO. 1; SODIUM CITRATE; TITANIUM DIOXIDE; ETHYL VANILLIN; FD&C YELLOW NO. 6

Dothelle DHA

STATEMENT OF IDENTITY:

Dothelle DHA is an orally administered prescription dietary supplement and should be administered under the supervision of a licensed medical practitioner.

WARNING:

Accidental overdose of iron-containing products is a leading cause of fatal poisoning in children under 6. Keep this product out of reach of children. In case of accidental overdose, call a doctor or poison control center immediately.

DOSAGE AND ADMINISTRATION:

Adults (persons over 12 years of age), One (1) capsule daily, between meals, or as prescribed by a physician. Do not exceed recommended dosage. Do not administer to children under the age of 12.

Supplement Facts

Servings per Bottle: 30

Serving Size: 1 Capsule %DV for Pregnant

Each Capsule contains and Lactating Women

Ferrous Fumarate (anhydrous) 53.5 mg

(Equiv. to about 17.5 mg of Elemental Iron)

Polysaccharide Iron Complex 38 mg 194%¶

(Equiv. to about 17.5 mg of Elemental Iron)

Vitamin C* 25 mg 42%

Folic Acid 1 mg 125%

Vitamin B1 (thiamine mononitrate) 2 mg 118%

Vitamin B2 (riboflavin) 3 mg 150%

Vitamin B3* 1.8 mg 9%

Vitamin B5 (d-calcium pantothenate) 5 mg 50%

Vitamin B6 (pyridoxine HCl) 25 mg 1000%

Vitamin B7 (biotin) 300 mcg 100%

Vitamin B12 (cyanocobalamin) 12.5 mcg 156%

Copper (as copper sulfate) 2 mg 100%

Magnesium (as magnesium sulfate) 5 mg 1%

Zinc (as zinc sulfate) 10 mg 67%

Omega-3 Fatty acids† 200 mg ‡

DHA (docosahexaenoic acid) 156 mg ‡

EPA (eicosapentaenoic acid) 39 mg ‡

* Also containing Ascorbic Acid Precursors as (1) Acid Metabolites including niacinamide ascorbate, calcium ascorbate, magnesium ascorbate, potassium ascorbate and sodium ascorbate (2) Basic Amino Acids including lysine acetate; (3) Flavonoids including hesperidin; and (4) Glutathione.

¶ Total Iron: Ferrous Fumarate + Polysaccharide Iron Complex.

† At least 200 mg Omega-3 Fatty Acids derived from 310 mg fish oil. ‡ Daily value not established.

ALSO CONTAINS: Gelatin, Glycerin, Soy Lecithin, Yellow Beeswax, Natural Creamy Orange Flavour, L-Lysine Acetate, Hesperidin Complex, D&C Blue # 1, Sodium Citrate, Titanium Dioxide, Ethyl Vanillin, L-Glutathione, FD&C Yellow # 6.

HOW SUPPLIED: The Dothelle DHA capsule is an oval, blue soft gelatin capsule, and is imprinted with "M121". Dothelle DHA is dispensed in child-resistant bottles of 30 capsules.

PRECAUTIONS/WARNING:

WARNING: Ingestion of more than 3 grams of omega-3 fatty acids from fish oils per day may have potential antithrombotic effects, including an increased bleeding time and INR (International Normalized Ratio). Omega-3 fatty acids from fish oils (e.g., DHA) should be avoided in patients with inherited or acquired bleeding diatheses, including those taking anticoagulants.

WARNING: Folic acid alone is improper therapy in the treatment of pernicious anemia and other megaloblastic anemias where vitamin B12 is deficient.

PRECAUTIONS

General: Folic acid in doses above 0.1 mg daily may obscure pernicious anemia, in that hematologic remission can occur while neurological manifestations remain progressive.

Pediatric Use: Safety and effectiveness of this product have not been established in pediatric patients.

Geriatric Use: No clinical studies have been performed in patients 65 and older to determine whether older persons respond differently from younger persons. Dosage should always begin at the low end of the dosage scale and should consider that elderly persons may have decreased hepatic, renal, or cardiac function and/or concomitant diseases.

STORAGE: Store at 20°-25° C (68°-77° F). Excursions permitted to 15°-30° C (59°-86° F). [See USP Controlled Room Temperature]. Protect from light and moisture. Dispense in a tight, light-resistant container.

HEALTH CLAIMS:

Prescription Vitamin B9 Containing Dietary Supplement

PRINCIPAL DISPLAY PANEL

NDC 58657-121-30
Dothelle DHA
Softgels
Rx
30 Capsules